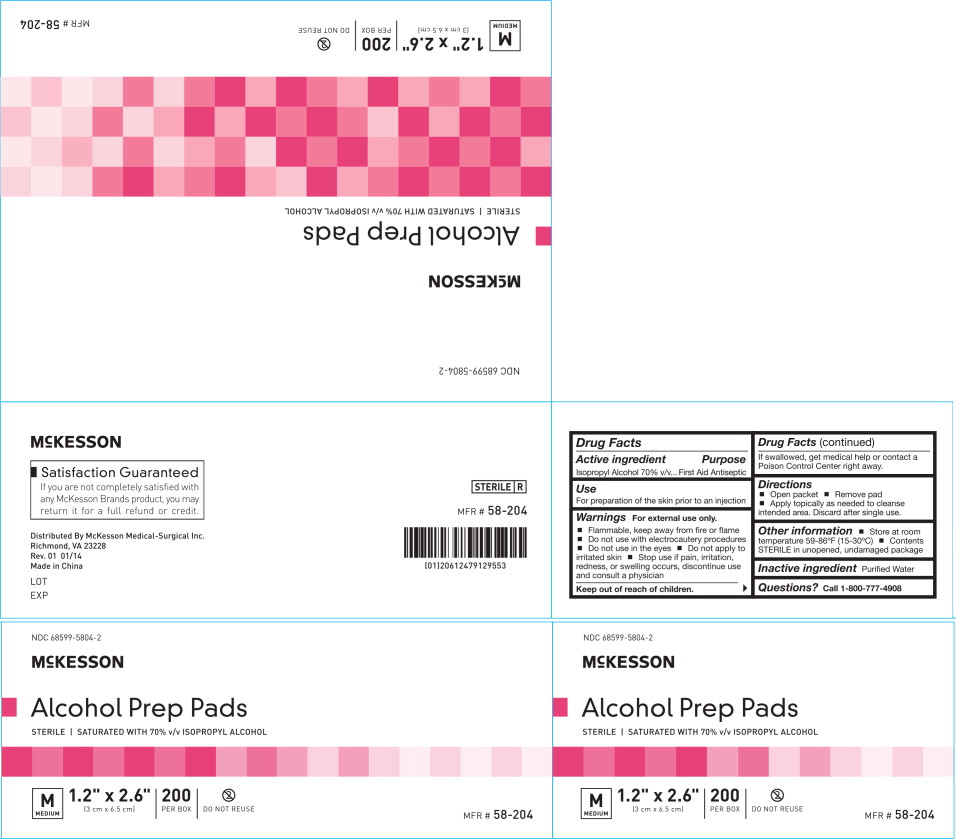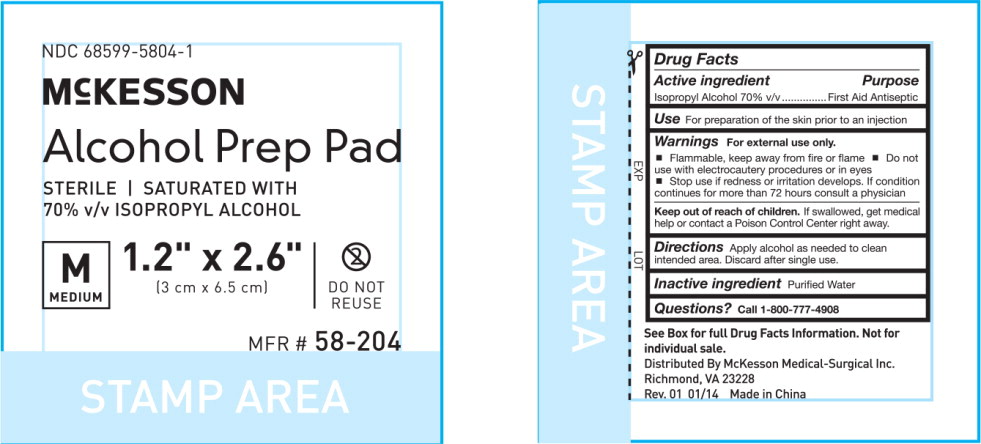 DRUG LABEL: McKesson Alcohol Prep Pad
NDC: 68599-5804 | Form: SWAB
Manufacturer: McKesson Medical-Surgical
Category: otc | Type: HUMAN OTC DRUG LABEL
Date: 20260113

ACTIVE INGREDIENTS: ISOPROPYL ALCOHOL 0.7 mL/1 mL
INACTIVE INGREDIENTS: WATER

McKesson Alcohol Prep Pads

Drug Facts

Active ingredient

Isopropyl Alcohol 70% v/v

Purpose

First Aid Antiseptic

Use

For preparation of the skin prior to an injection

Warnings

- For external use only
- Flammable, keep away from fire or flame

- Do not use with electrocautery procedures
- Do not use in the eyes
- Do not apply to irritated skin

- Stop use if pain, irritation, redness, or swelling occurs, discontinue use and consult a physician.

KEEP OUT OF REACH OF CHILDREN

- Keep out from reach of children.If swallowed, get medical help or contact a Poison Control Center right away.

Directions

- Open packet
- Remove pad
- Apply topically as needed to cleanse intended area. Discard after single use.

Other information

- Store at room temperature 59-86°F (15-30°C)
- Contents sterile in unopened, undamaged package

Inactive ingredients

purified water

Principal Display Panel – Box Label

NDC 68599-5804-2

MCKESSON

Alcohol Prep Pads

STERILE | SATURATED WITH 70% v/v ISOPROPYL ALCOHOL

1.2" x 2.6"
(3 cm x 6.5 cm)

200
PER BOX

DO NOT REUSE

MFR# 58-204

Principal Display Panel – Packet Label

NDC 68599-5804-1

MCKESSON

Alcohol Prep Pad

STERILE | SATURATED WITH
70% v/v ISOPROPYL ALCOHOL

1.2" x 2.6"
(3 cm x 6.5 cm)

DO NOT
REUSE

MFR# 58-204